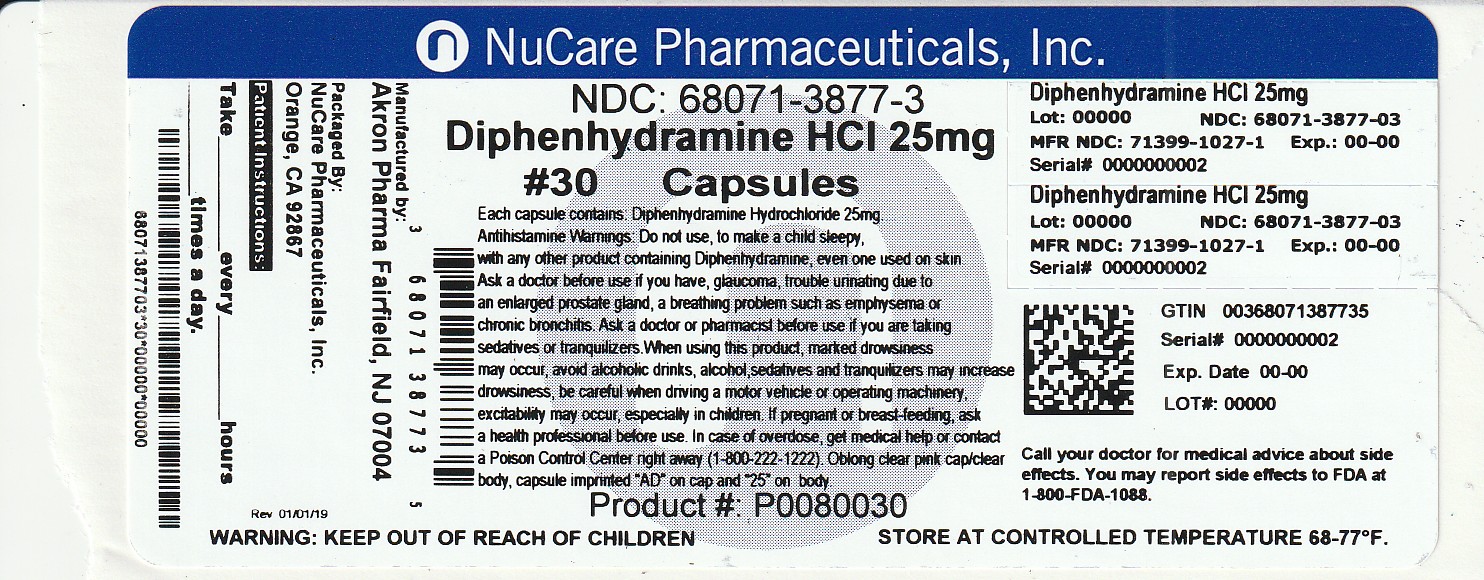 DRUG LABEL: Diphenhydramine HCl
NDC: 68071-3877 | Form: CAPSULE
Manufacturer: NuCare Pharmaceuticals,Inc.
Category: otc | Type: HUMAN OTC DRUG LABEL
Date: 20260105

ACTIVE INGREDIENTS: DIPHENHYDRAMINE HYDROCHLORIDE 25 mg/1 1
INACTIVE INGREDIENTS: SILICON DIOXIDE; GELATIN; LACTOSE MONOHYDRATE; MAGNESIUM STEARATE; MICROCRYSTALLINE CELLULOSE

Akron Pharma, Inc.

Active ingredient (in each banded capsule)

Diphenhydramine Hydrochloride 25 mg and 50 mg

Purpose

Antihistamine

Uses

temporarily relieves these symptoms due to hay fever or other upper respiratory allergies:

- runny nose
- sneezing
- itchy, watery eyes
- itching of the nose or throat

Warnings

Do not use

- to make a child sleepy
- with any other product containing diphenhydramine, even one used on skin

Ask a doctor before use if you have

- glaucoma
- difficulty in urination due to enlargement of the prostate gland
- a breathing problem such as emphysema or chronic bronchitis

Ask a doctor or pharmacist before use if you are

taking sedatives or tranquilizers.

When using this product

- marked drowsiness may occur
- avoid alcoholic beverages
- alcohol, sedatives, and tranquilizers may increase drowsiness
- excitability may occur, especially in children
- be careful when driving a motor vehicle or operating machinery

If pregnant or breast-feeding,

ask a health professional before use.

Keep out of reach of children.

In case of overdose, get medical help or contact a Poison Control Center (1-800-222-1222) right away.

Directions

- take every 4 to 6 hours
- do not take more than 6 doses in 24 hours

25 mg Dosage:

Age | Dose
adults and children 12 years and over | 1 to 2 capsules
children 6 to under 12 years of age | 1 capsule
children under 6 years of age | do not use this product in children under 6 years of age

50 mg Dosage:

Age | Dose
adults and children 12 years and over | 1 capsules
children under 12 years of age | ask a doctor, the proper dosage strength is not available in this package**

**Do not attempt to break capsules. The proper dosage strength and dosing information for children under 12 years of age is available on the
25 mg. package.

Other information

- store at temperature 15° to 30° C (59° to 86°F)
- do not use if either capsule band or imprinted safety seal under cap is broken or missing
- protect from moisture

Inactive ingredients

Colloidal silicon dioxide, Gelatin, Lactose Monohydrate, Magnesium Stearate, Microcrystalline cellulose

Questions or comments?

Call toll-free 1-877-225-6999

Manufactured for:
Akron Pharma, Inc,

373 RT US 46 W, Building E,

Suite 117, Fairfield, NJ 07004